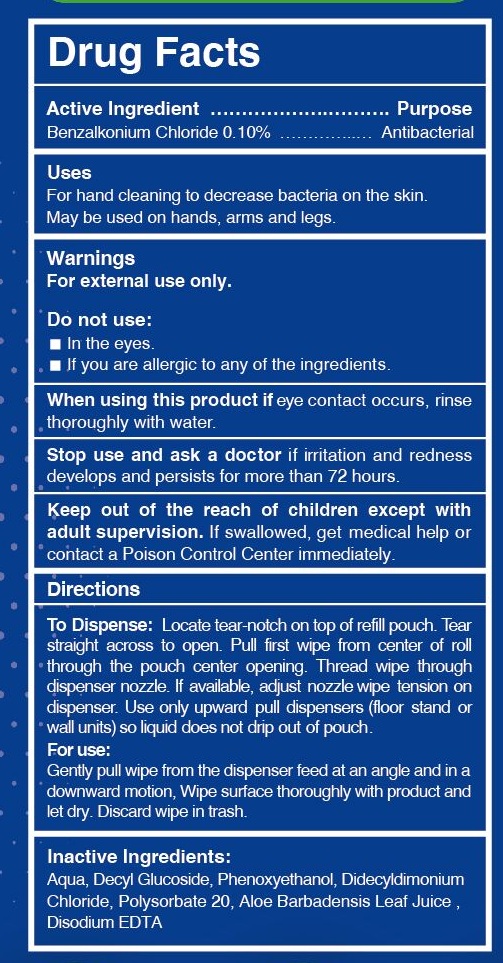 DRUG LABEL: Antibacterial Wet Wipes
NDC: 79237-001 | Form: CLOTH
Manufacturer: Jiaxing Hongjie Commodity Co.,Ltd.
Category: otc | Type: HUMAN OTC DRUG LABEL
Date: 20211102

ACTIVE INGREDIENTS: BENZALKONIUM CHLORIDE 0.1 1/100 1
INACTIVE INGREDIENTS: PHENOXYETHANOL; DECYL GLUCOSIDE; WATER; DIDECYLDIMONIUM CHLORIDE; POLYSORBATE 20; EDETATE DISODIUM

ACTIVE INGREDIENT

Benzalkonium Chloride 0.10%.........................Antibacterial

DOSAGE AND ADMINISTRATION

For use:

Gently pull wipe from the dispenser feed at an angle and in a downward motion, Wipe surface throughly with product and let dry. Discard wipe in trash.

PURPOSE

For hand cleaning to decrease bacteria on the skin. May be on hands, arms and legs.

KEEP OUT OF REACH OF CHILDREN

Keep out of the reach of children except with adults supervision. If swallowed, get medical help or contact a Poison Control Center immediately.

WARNINGS

For external use only.

Do not use:

In the eyes.

If you are allergic to any of the ingredients.

When using the product if eye contact occours, rinse thoroughly with water.

Stop and ask a doctor if irritation and redness develops and presists for more than 72 hours.

INACTIVE INGREDIENT

Aqua, Decly Glucoside, Phenoxyethanol, Didecyldimonium Chloride, Polysorbate 20, Aloe Barbadensis Leaf Juice, Disodium EDTA

INDICATIONS AND USAGE

For hand cleaning to decrease bacteria on the skin. May br used on hands, arms and legs